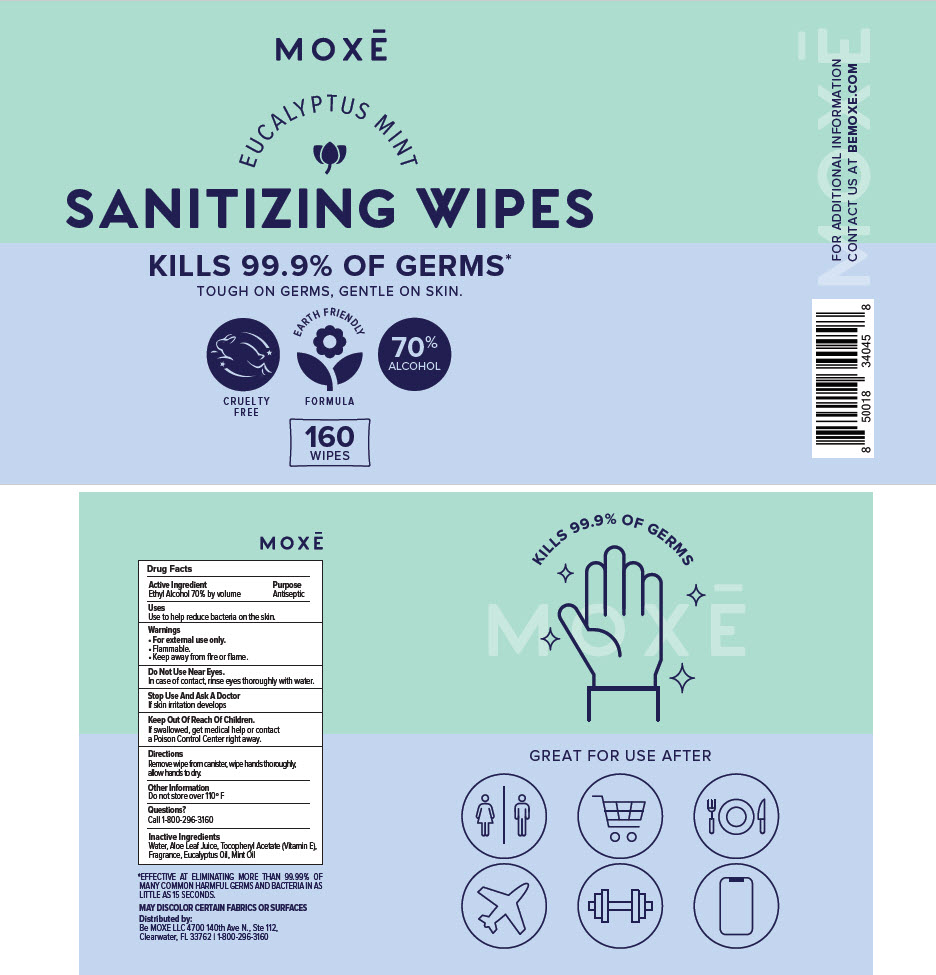 DRUG LABEL: EUCALYPTUS MINT SANITIZING WIPES
NDC: 75435-160 | Form: CLOTH
Manufacturer: Be Moxe, LLC
Category: otc | Type: HUMAN OTC DRUG LABEL
Date: 20201020

ACTIVE INGREDIENTS: Alcohol 70 mL/100 mL
INACTIVE INGREDIENTS: WATER; ALOE; .ALPHA.-TOCOPHEROL; EUCALYPTUS OIL

EUCALYPTUS MINT SANITIZING WIPES

Drug Facts

Active Ingredient

Ethyl Alcohol 70% by volume

Purpose

Antiseptic

Uses

Use to help reduce bacteria on the skin.

Warnings

- For external use only.
- Flammable.
- Keep away from fire or flame.

Do Not Use Near Eyes.

In case of contact, rinse eyes thoroughly with water.

Stop Use And Ask A Doctor

If skin irritation develops

Keep Out Of Reach Of Children.

If swallowed, get medical help or contact a Poison Control Center right away.

Directions

Remove wipe from canister, wipe hands thoroughly, allow hands to dry.

Other Information

Do not store over 110º F

Questions?

Call 1-800-296-3160

Inactive Ingredients

Water, Aloe Leaf Juice, Tocopheryl Acetate (Vitamin E), Fragrance, Eucalyptus Oil, Mint Oil

Distributed by:
Be MOXĒ LLC 4700 140th Ave N., Ste 112,
Clearwater, FL 33762

PRINCIPAL DISPLAY PANEL - 160 Wipe Canister

MOXĒ

EUCALYPTUS MINT

SANITIZING WIPES

KILLS 99.9% OF GERMS*
TOUGH ON GERMS, GENTLE ON SKIN.

CRUELTY
FREE

EARTH FRIENDLY
FORMULA

70%
ALCOHOL

160
WIPES